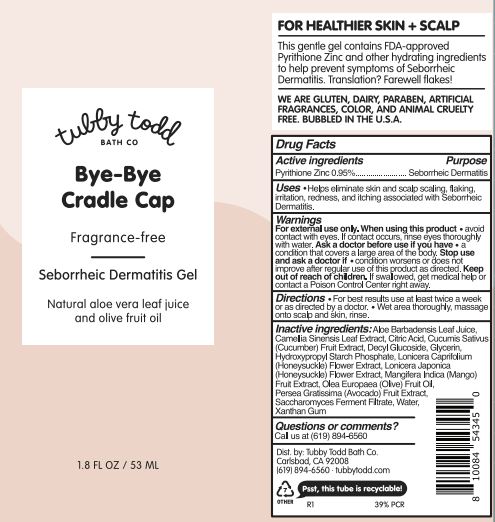 DRUG LABEL: BYE-BYE CRADLE CAP
NDC: 73088-401 | Form: GEL
Manufacturer: Tubby Todd
Category: otc | Type: HUMAN OTC DRUG LABEL
Date: 20241212

ACTIVE INGREDIENTS: PYRITHIONE ZINC 0.95 g/100 mL
INACTIVE INGREDIENTS: LONICERA JAPONICA FLOWER; WATER; ANHYDROUS CITRIC ACID; SACCHAROMYCES LYSATE; ALOE VERA LEAF; CUCUMBER; MANGO; LONICERA CAPRIFOLIUM FLOWER; OLIVE OIL; HYDROXYPROPYL CORN STARCH (5% SUBSTITUTION BY WEIGHT); GREEN TEA LEAF; DECYL GLUCOSIDE; XANTHAN GUM; GLYCERIN; AVOCADO

Tubby Todd (as PLD) - Bye-Bye Cradle Cap (73088-401)

Active Ingredients

PYRITHIONE ZINC 0.95%

Purpose

SEBORRHEIC DERMATITIS

Uses

Helps eliminate skin and scalp scaling, flaking, irritation, redness, and itching associated with Seborrheic Dermatitis.

Warnings

For External Use Only

When using this product

- Avoid contact with eyes. If contact occurs, rinse thoroughly with water.
- Ask a doctor before use if you have a condition that covers a large area of the body.
- Stop use and ask a doctor if condition worsens or does not improve after regular use of this product as directed.
- Keep out of reach of children.
- If swallowed, get medical help or contact Poison Control Center right away.

Keep out of reach of children. If swollowed, get medical help or contact a Poison Control Center right away.

Directions

For best results use at least twice a week or as directed by a doctor. Wet area thoroughly, massage onto scalp and skin, rinse.

Other Information

- Do not use if quality seal is broken or missing
- Protect from excessive heat (40°C/104°F)

Inactive ingredients

Lavender and Rosemary: Beeswax, Camellia Sinensis Leaf Extract*, Caprylic/Capric Triglyceride, Cetyl Alcohol, Cucumis Sativus (Cucumber) Fruit Extract*, Fragrance**, Glycerin, Jojoba Esters, Lavandula Angustifolia (Lavender) Oil, Lavandula Hybrida (Lavandin) Oil, Lonicera Caprifolium (Honeysuckle) Flower Extract, Lonicera Japonica (Honeysuckle) Flower Extract, Mangifera Indica (Mango) Fruit Extract*, Persea Gratissima (Avocado) Fruit Extract*, Propanediol, Saccharomyces Ferment Filtrate, Stearic Acid, Stearyl Alcohol, Water

*Organic ingredient

**Comprised of natural, aromatic, raw materials

Questions or comments?

Call us at (619) 894-6560